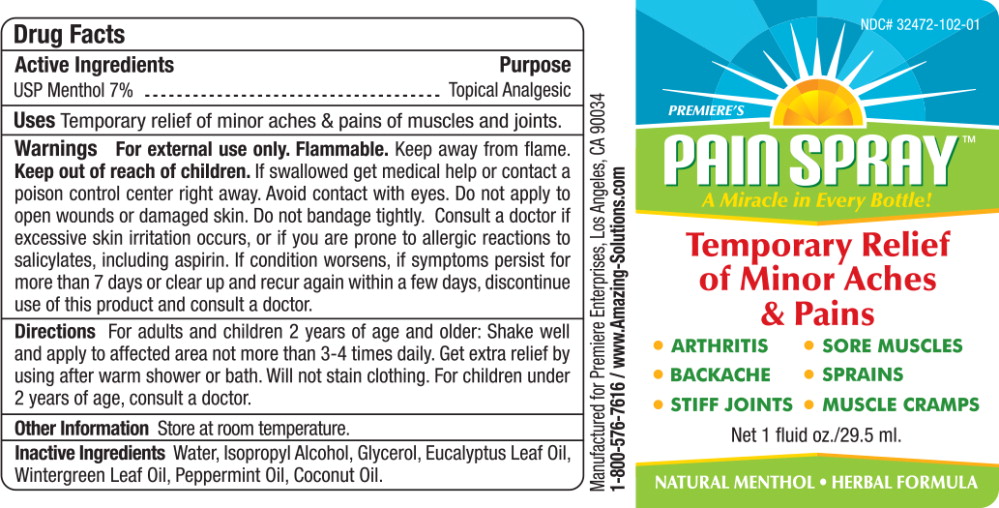 DRUG LABEL: Premieres Pain
NDC: 32472-102 | Form: SPRAY
Manufacturer: Premiere Enterprises
Category: otc | Type: HUMAN OTC DRUG LABEL
Date: 20251223

ACTIVE INGREDIENTS: MENTHOL 7 g/100 mL
INACTIVE INGREDIENTS: WATER; ISOPROPYL ALCOHOL; GLYCERIN; EUCALYPTUS OIL; METHYL SALICYLATE; PEPPERMINT OIL; COCONUT OIL

Analgesic

PREMIERE'S PAIN SPRAY
Premiere Enterprises, Inc.

Pain Spray

Drug Facts

Active Ingredients

USP Menthol 7%

Purpose

Topical Analgesic

Uses:

Temporary relief of minor aches & pains of muscles and joints.

Warnings:

- For external use only
- Flammable.Keep away from flame.

- Keep out of reach of children-if swallowed get medical help or contact a poison center right away.
- Avoid contact with eyes
- Do not apply to open wounds or damaged skin
- Do not bandage tightly

ASK DOCTOR

- Consult a doctor if excessive skin irritation occurs, or if you are prone to allergic reactions to salicylates, including aspirin. If condition worsens, if symptoms persist for more than 7 days or clear up and recur again within a few days, discontinue use of this product and consult a doctor.

Directions:

For adults and children 2 years of age and older: Shake well and apply to affected area not more than 3-4 times daily. Get extra relief by using after warm shower or bath. Will not stain clothing. For children under 2 years of age, consult a doctor.

Other Information:

Store at room temperature.

Inactive Ingredients:

Water, Isopropyl Alcohol, Glycerol, Eucalyptus Leaf Oil, Wintergreen Leaf Oil, Peppermint Oil, Coconut Oil.

Manufactured for: PREMIERE ENTERPRISES,Los Angeles, CA 90034
800-576-7616/ www.Amazing-Solutions.com

Principal Display Panel - Bottle Label

NDC# 32472-102-01

PREMIER'S

PAIN SPRAY™

A Miracle in Every Bottle!

Temporary Relief
of Minor Aches
& Pains

• ARTHRITIS • SORE MUSCLES

• BACKACHE • SPRAINS

• STIFF JOINTS • MUSCLE CRAMPS

Net 1 fluid oz./29.5 ml.

NATURAL MENTHOL • HERBAL FORMULA